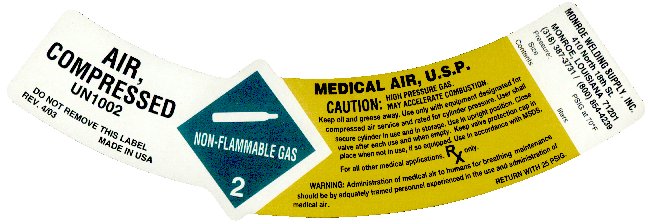 DRUG LABEL: medical air
NDC: 52233-005 | Form: GAS
Manufacturer: Monroe Welding Supply, Inc.
Category: prescription | Type: HUMAN PRESCRIPTION DRUG LABEL
Date: 20100824

ACTIVE INGREDIENTS: oxygen 210 mL/1 L; nitrogen 790 mL/1 L

PACKAGE LABEL

AIR, COMPRESSED
UN 1002
DO NOT REMOVE THIS LABEL REV. 4/03 MADE IN USA
MEDICAL AIR, USP
CAUTION: HIGH PRESSURE GAS. MAY ACCELERATE COMBUSTION. Keep oil and grease away. Use only with equipment designed for compressed air service and rated for cylinder pressure. User shall secure cylinder in use and in storage. Use in upright position. Close valve after each use and when empty. Keep valve protection cap in place when not in use, if so equipped. Use in accordance with MSDS. For all other medical applications, Rx only.
WARNING: Administration of medical air to humans for breathing maintenance should be by adequately trained personnel experienced in the use and administration of medical air.
RETURN WITH 25 PSIG
MONROE WELDING SUPPLY, INC.
410 N 18TH STREET MONROE, LA 71201
318-387-3731 / 1-800-854-4239
Pressure: PSIG AT 70F
Size
Contents liters